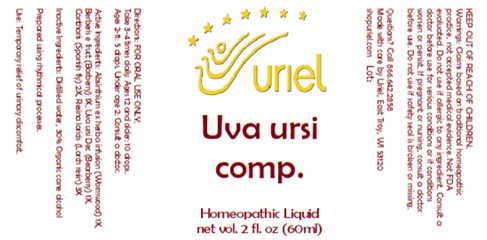 DRUG LABEL: Uva ursi comp.
NDC: 48951-9389 | Form: LIQUID
Manufacturer: Uriel Pharmacy, Inc
Category: homeopathic | Type: HUMAN OTC DRUG LABEL
Date: 20250120

ACTIVE INGREDIENTS: ARCTOSTAPHYLOS UVA-URSI LEAF 1 [hp_X]/1 mL; WORMWOOD 1 [hp_X]/1 mL; BERBERIS VULGARIS ROOT BARK 1 [hp_X]/1 mL; LYTTA VESICATORIA 2 [hp_X]/1 mL; LARIX DECIDUA RESIN 3 [hp_X]/1 mL
INACTIVE INGREDIENTS: ALCOHOL; WATER

Uva uris comp.

INDICATIONS AND USAGE

Directions: FOR ORAL USE ONLY.

DOSAGE AND ADMINISTRATION

Take 3-4 times daily. Ages 12 and older: 10 drops.
Ages 2-11: 5 drops. Under age 2: Consult a doctor.

ACTIVE INGREDIENT

Active Ingredients: Absinthium ex herba infusion (Wormwood) 1X, Berberis e fruct (Barberry) 1X, Uva ursi Dec (Bearberry) 1X, Cantharis (Spanish fly) 2X, Resina laricis (Larch resin) 3X

Inactive Ingredients: Distilled water, 30% Organic cane alcohol

Prepared using rhythmical processes.

PURPOSE

Use: Temporary relief of urinary discomfort.

KEEP OUT OF REACH OF CHILDREN.

WARNINGS

Warnings: Claims based on traditional homeopathic practice, not accepted medical evidence. Not FDA evaluated. Do not use if allergic to any ingredient. Consult a doctor before use for serious conditions or if conditions worsen or persist. If pregnant or nursing, consult a doctor before use. Do not use if safety seal is broken or missing.

Questions? Call 866.642.2858
Made with care by Uriel, East Troy, WI 53120
shopuriel.com Lot: